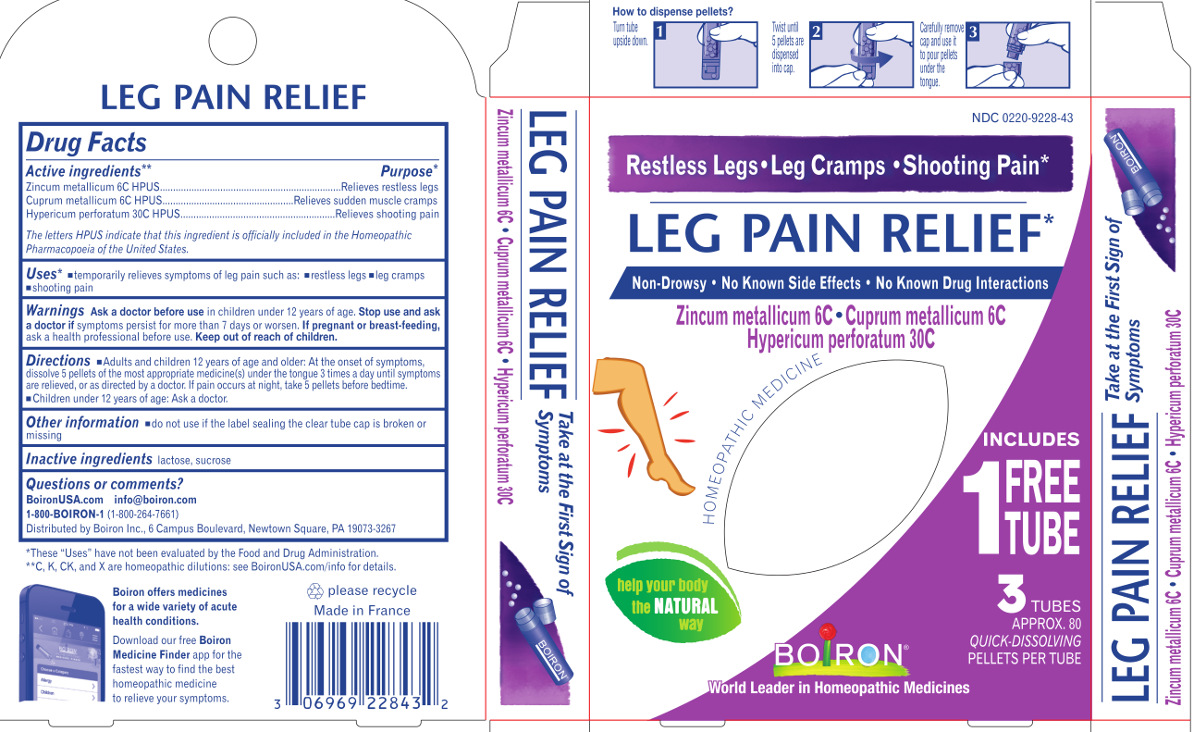 DRUG LABEL: Leg Pain Relief
NDC: 0220-9228 | Form: PELLET
Manufacturer: Laboratoires Boiron
Category: homeopathic | Type: HUMAN OTC DRUG LABEL
Date: 20231004

ACTIVE INGREDIENTS: ZINC 6 [hp_C]/1 1; COPPER 6 [hp_C]/1 1; HYPERICUM PERFORATUM 30 [hp_C]/1 1
INACTIVE INGREDIENTS: SUCROSE; LACTOSE

Leg Pain Relief

Active Ingredients**

Zincum metallicum 6C HPUS
Cuprum metallicum 6C HPUS
Hypericum perforatum 30C HPUS
The letters HPUS indicate that this ingredient is officially included in the Homeopathic Pharmacopoeia of the United States.

Purpose*

Zincum metallicum 6C HPUS ..... Relieves restless legs
Cuprum metallicum 6C HPUS ..... Relieves sudden muscle cramps
Hypericum perforatum 30C HPUS ..... Relieves shooting pain

Uses*

temporarily relieves symptoms of leg pain such as: restless legs, leg cramps, shooting pain

Warnings

Ask a doctor before usein children under 2 years of age.

Stop use and ask a doctor if

symptoms persist for more than 7 days or worsen.

If pregnant or breast-feeding,

ask a health professional before use.

Directions

Adults and children 2 years of age and older: At the onset of symptoms, dissolve 5 pellets of the most appropriate medicine(s) under the tounge 3 times a day until symptoms are releived, or as directed by a doctor. If pain occurs at night, take 5 pellets before bedtime.
Children under 2 years of age: Ask a doctor.

Other information

do not used if the label sealing the clear tube cap is broken or missing

Inactive ingredients

lactose, sucrose

Questions, Comments?

BoironUSA.com
info@boiron.com
1-800-BOIRON-1 (1-800-264-7661)
Distributed by Boiron Inc., 6 Campus Boulevard, Newtown Square, PA 19073-3267

Notes:

*These "Uses" have not been evaluated by the Food And Drug Administration.
**C, K, CK and X are homeopathic dilutions: see BoironUSA.com/info for details.